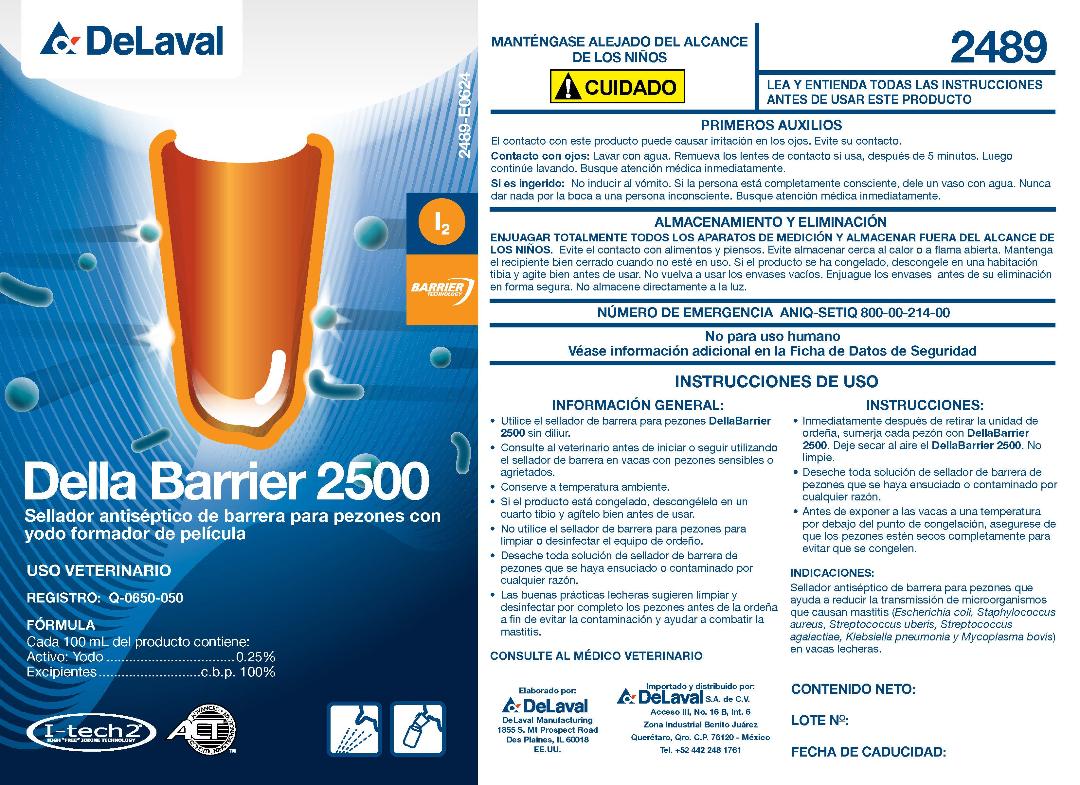 DRUG LABEL: Della Barrier 2500
NDC: 55756-489 | Form: SOLUTION
Manufacturer: DeLaval
Category: animal | Type: OTC ANIMAL DRUG LABEL
Date: 20240808

ACTIVE INGREDIENTS: IODINE .0025 g/1 L
INACTIVE INGREDIENTS: GLYCERIN; SODIUM HYDROXIDE; ANHYDROUS CITRIC ACID; XANTHAN GUM; POVIDONE K30; POLOXAMER 335; SORBITOL SOLUTION 70%; SODIUM CHLORIDE; SODIUM IODATE; WATER

Della Barrier 2500TM

Della Berrier 2500

Sellador antiséptico de barrera para pezones con yodo formador de película

USO VETERINARIO

REGISTRO: Q-0650-050

ACTIVE INGREDIENT

FÓRMULA

Cada 100 mL del producto contiene:

Activo: Yodo..............................0.25%

Excipientes.......................c.b.p. 100%

KEEP OUT OF REACH OF CHILDREN

MANTÉNGASE ALEJADO DEL ALCANCE DE LOS NINOS

! CUIDADO

LEA Y ENTIENDA TODAS LAS INSTRUCCIONES ANTES DE USAR ESTE PRODUCTO

READ AND UNDERSTAND ALL INSTRUCTIONS BEFORE USING THIS PRODUCT

FIRST AID

Contact with product can cause irritation to eyes. Avoid contact with eyes.

If in Eyes: Flush with water. Remove contact lenses, if present, after first 5 minutes. Then continue rinsing. Get immedicate medical attention.

If Swallowed: Do not induce vomiting. If victim is fully conscious, give a cupful of water. Never give anything by mouth to an unconscious person. Get immediate medical attention.

STORAGE AND DISPOSAL

THOROUGHLY RINSE ALL MEASURING DEVICES AND STORE OUT OF REACH OF CHILDREN. Avoid contact with food or feed. Avoid storing near heat or open flame. Keep container tightly closed when not in use. If product has frozen, thaw in a warm room and shake well before use. Do not reuse empty container. Rinse empty container before disposing of in a safe manner. Do not store in direct sunlight.

NÚMERO DE EMERGENCIA ANIQ-SETIQ 800-00-214-00

WARNINGS

No para uso humano

Véase información adicional en la Ficha de Datos de Seguridad

INDICATIONS AND USAGE

GENERAL INSTRUCTIONS

- Use Della Barrier 2500TM teat sanitizer undiluted.
- Consult veterinarian before starting or continuing to use teat dip if cow's teats are sore or chapped.
- Store at room temperature.
- Do not use teat sanitizer for cleaning or sanitizing dairy equipment.
- Discard any teat sanitizer solution that becomes dirty or contaminated for any reason.
- Good dairy practices suggest the thorough cleaning and sanitizing of teats before milking to avoid contamination and assist in control of mastitis.

POST-DIPPING

- Immediately after removing milker unit, dip each teat with Della Barrier 2500TM
- Allow Della Barrier 2500TM to air dry. Do not wipe off.
- Do not expose teats to freezing conditions until they are dry.

INDICACIONES:

Sellador antiséptico de barrera para pezones que ayuda a reducir la transmissión de microoranismosque causan mastitis (Escherichia coli, Staphylococcus aureus, Steptococcus uberis, Streptococcus agalactiae, Klebsiella pheumonia y Mycoplasma bovis) en vacas lecheras.

CONSULTE AL MEDICO VETERINARIO

CONTENIDO NETO:

LOTE Nο:

FECHA DE CADUCIDAD:

PACKAGE LABEL

Add image transcription here...